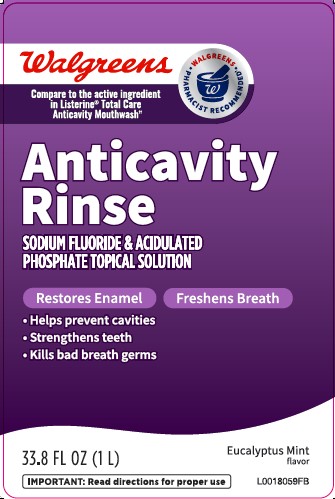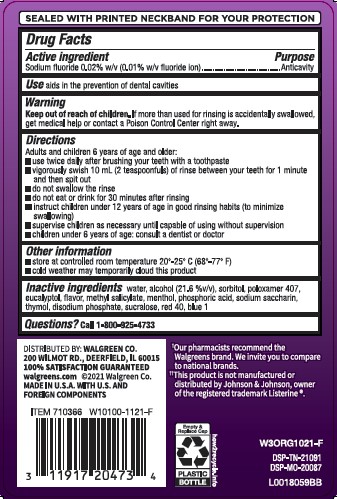 DRUG LABEL: Mouth Rinse
NDC: 0363-0163 | Form: MOUTHWASH
Manufacturer: Walgreen Co.
Category: otc | Type: HUMAN OTC DRUG LABEL
Date: 20260212

ACTIVE INGREDIENTS: SODIUM FLUORIDE 0.1 mg/1 mL
INACTIVE INGREDIENTS: WATER; ALCOHOL; SORBITOL; POLOXAMER 407; EUCALYPTOL; METHYL SALICYLATE; MENTHOL; PHOSPHORIC ACID; SACCHARIN SODIUM; THYMOL; SODIUM PHOSPHATE, DIBASIC, ANHYDROUS; SUCRALOSE; FD&C RED NO. 40; FD&C BLUE NO. 1

Walgreens 163.005/163AF-AG
Anticavity Mouth Rinse

Active Ingredient

Sodium fluoride 0.02% w/v (0.01% w/v fluoride ion)

Purpose

Anticavity

Use

aids in the prevention of dental cavities

Warnings

for this product

Keep out of reach of children.

If more than used for rinsing is accidentally swallowed, get medical help or contact a Poison Control Center right away.

Directions

Adults and children 6 years of age and older:

- use twice daily after brushing your teeth with a toothpaste
- vigorously swish 10 mL (2 teaspoonfuls) of rinse between your teeth for 1 minute and then spit out
- do not swallow the rinse
- do not eat or drink anything for 30 minutes after rinsing
- instruct children under 12 years of age in good rinsing habits (to minimize swallowing)
- supervise children as necessary until capable of using without supervision
- children under 6 years of age: consult a dentist or doctor

Other information

- store at controlled room temperature 20⁰ - 25⁰C (68⁰ - 77⁰ F)
- cold weather may temporarily cloud this product

Inactive ingredients

water, alcohol (21.6 %v/v), sorbitol, poloxamer 407, eucalyptol, flavor, methyl salicylate, menthol, phosphoric acid, sodium saccharin, thymol, disodium phosphate, sucralose, red 40, blue 1

Questions

Call 1-800-925-4733

Disclaimers

†Our pharmacists recommend the Walgreens brand. We invite you to compare to national brands.

‡This product is not manufactured or distributed by Johnson & Johnson Healthcare Products, owner of the registered trademark Listerine.

ADVERSE REACTION

DISTRIBUTED BY: WALGREEN CO.

200 WILMOT RD, DEERFIELD, IL 60015

100% SATISFACTION GUARANTEED

walgreens.com ©2021 Walgreen Co.

MADE IN THE U.S.A. WITH U.S. AND FOREIGN COMPONENTS

Empty & Replace Cap

PLASTIC BOTTLE

how2recycle.info

DSP-TN-21091

DSP-MO-20087

principal display panel

Walgreens

WALGREENS PHARMACIST RECOMMENDED

Compare to the active ingredient in Listerine®Total Care Anticavity Mouthwash‡

Anticavity Rinse

SODIUM FLUORIDE & ACIDULATED PHOSPHATE TOPICAL SOLUTION

Restores Enamel

Freshens Breath

- Helps prevent cavities
- Strengthen teeth
- Kills bad breath germs

Eucalyptus Mint flavor

33.8 fl oz (1 L)

IMPORTANT: Read directions for proper use